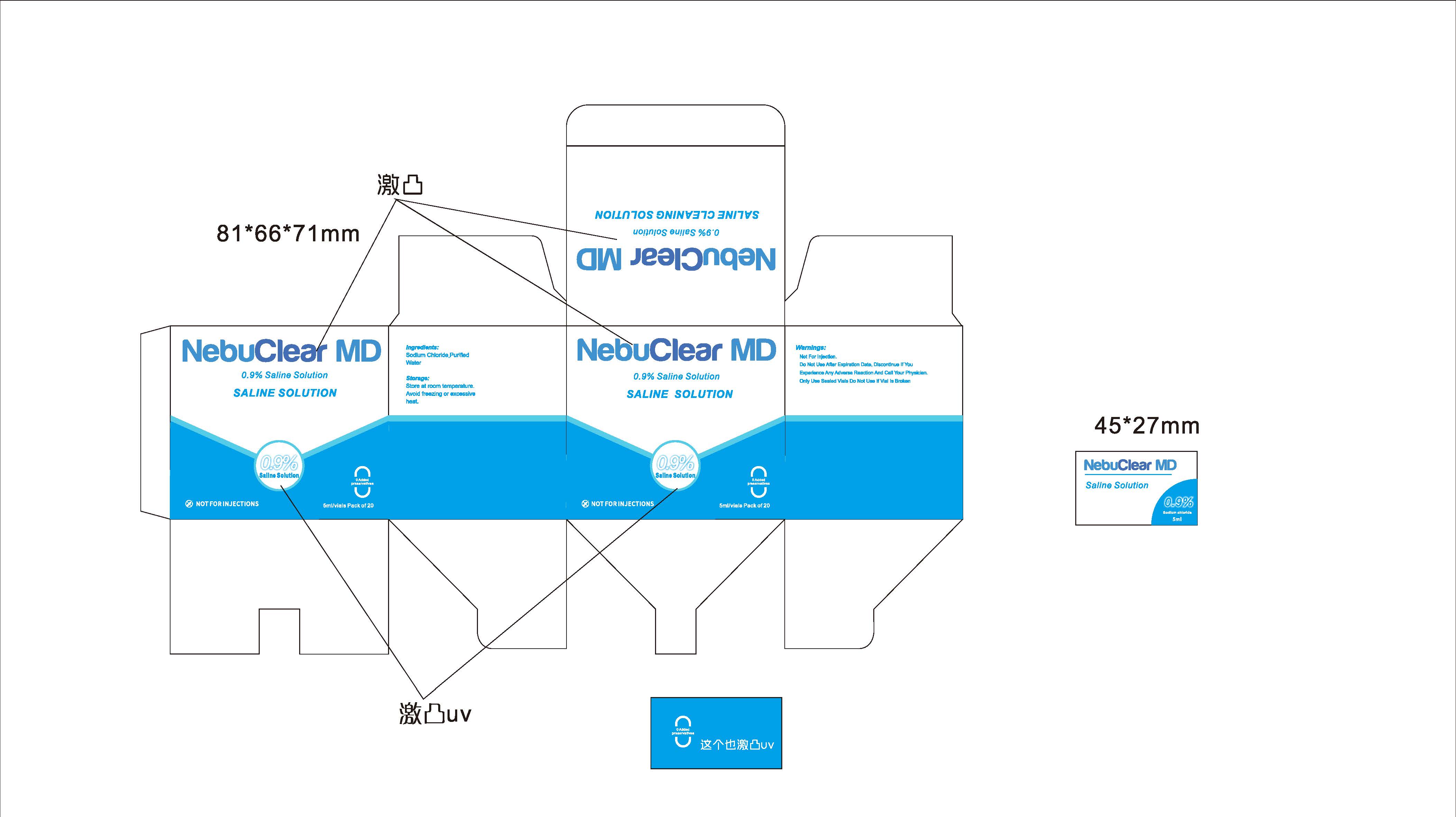 DRUG LABEL: NebuClear MD
NDC: 73117-520 | Form: LIQUID
Manufacturer: Blue Echo Care LLC
Category: otc | Type: HUMAN OTC DRUG LABEL
Date: 20250924

ACTIVE INGREDIENTS: SODIUM CHLORIDE 9 mg/9 mg
INACTIVE INGREDIENTS: WATER

ACTIVE INGREDIENT

.9% Sodium Chloride

PURPOSE

Saline for Inhalation

INDICATIONS AND USAGE

For moistening of the nasal, throat and lungs

WARNINGS

see a doctor if you:

- Get worse
- Need more than 12 inhalations in 24 hours
- Use more than 9 inhalations in 24 hours for 3 or more days a week
- Ever been hospitalized for asthma
- Heart disease
- High blood pressure
- Diabetes
- Thyroid disease
- Seizures

Keep out of reach of children.

Directions

- Do not use more than directed
- For use with a Nebulizer.
- Add 0.5 mL (contents of one vial) of solution to Nebulizer.

OTHER SAFETY INFORMATION

Protect from light. Avoid excessive heat. Protect from freezing.
Store between 2°C and 25°C (36°F and 77°F).
How Supplied: NebuClear MD® Saline Solution, .9$ Sodium Chloride, 5mL vials
20 vials

INACTIVE INGREDIENT

water

QUESTIONS

1 (855) 860-3404

support@blueechocare.com

Monday through Friday, 8:00 a.m. to 5:00 p.m. (Pacific Standard Time).

Manufactured By:

Blue Echo Care LLC
3639 SE 21st Ave

Portland, OR 97202 USA

PACKAGE LABEL

Contains 20 NebuClear MD® Saline vials